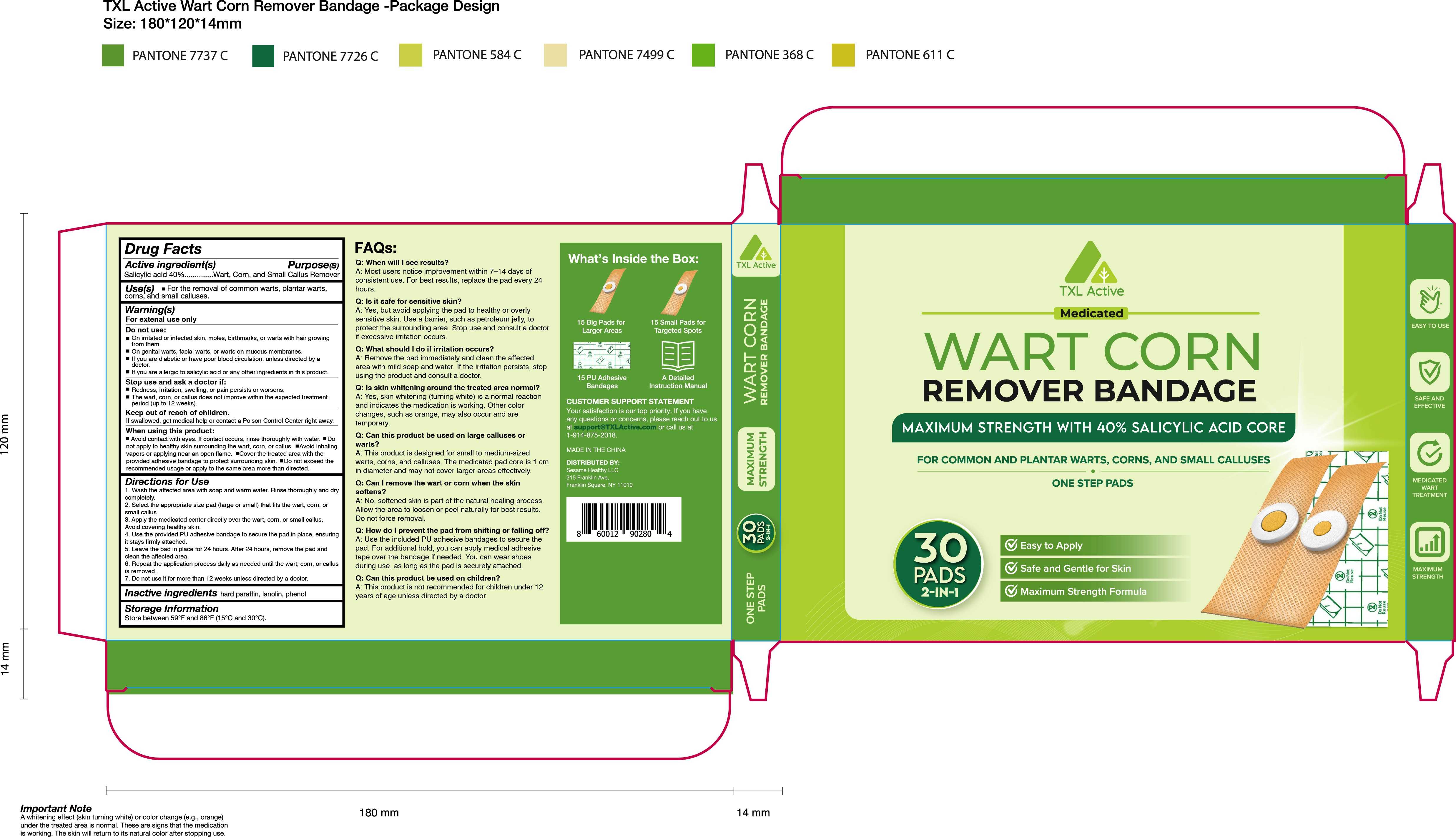 DRUG LABEL: TXL Active Wart Corn Remover Bandage
NDC: 83818-009 | Form: PATCH
Manufacturer: Shenzhen Xinxin Yunhai Technology Co., Ltd.
Category: otc | Type: HUMAN OTC DRUG LABEL
Date: 20241222

ACTIVE INGREDIENTS: SALICYLIC ACID 40 g/100 1
INACTIVE INGREDIENTS: PHENOL; PARAFFIN; LANOLIN

83818-009

Active Ingredient

Salicylic acid 40 %

Purpose

Wart, Corn and Small Callus Remover

Use

For the removal of common warts, plantar warts, corns, and small calluses.

Warnings

For external use only.

Do not use

On open wounds, irritated or infected skin,skin tags, moles, facial warts, genital warts,Molluscum, or milia (white bumps), or mucous membranes,

When Using

Avoid contact with eyes or healthy skin. In case of accidental contact, rinse thoroughly with water.

Stop Use

Redness, irritation, swelling, or pain persists or worsens.The wart, corn, or callus does not improve within the expected treatmentperiod (up to 12 weeks).

Ask Doctor

Redness, irritation, swelling, or pain persists or worsens.The wart, corn, or callus does not improve within the expected treatmentperiod (up to 12 weeks).

Keep Oot Of Reach Of Children

lf swallowed, get medical help or contact a Poison Control Center right away.

Directions

1.Wash the affected area with soap and warm water. Rinse thoroughly and drycompletely.
2. Select the appropriate size pad (large or small) that fits the wart, corn, orsmall callus.
3. Apply the medicated center directly over the wart, corn, or small callus.
Avoid covering healthy skin.4. Use the provided PU adhesive bandage to secure the pad in place, ensuring
it stays firmly attached.5. Leave the pad in place for 24 hours. After 24 hours, remove the pad andclean the affected area.
6. Repeat the application process daily as needed until the wart, corn, or callusis removed.
7. Do not use it for more than 12 weeks unless directed by a doctor.

Other information

store between 59° and 86°F (15°C and 30°C)

Inactive ingredients

Hard paraffin, lanolin, phenol

Questions

Call 1-914-875-2018